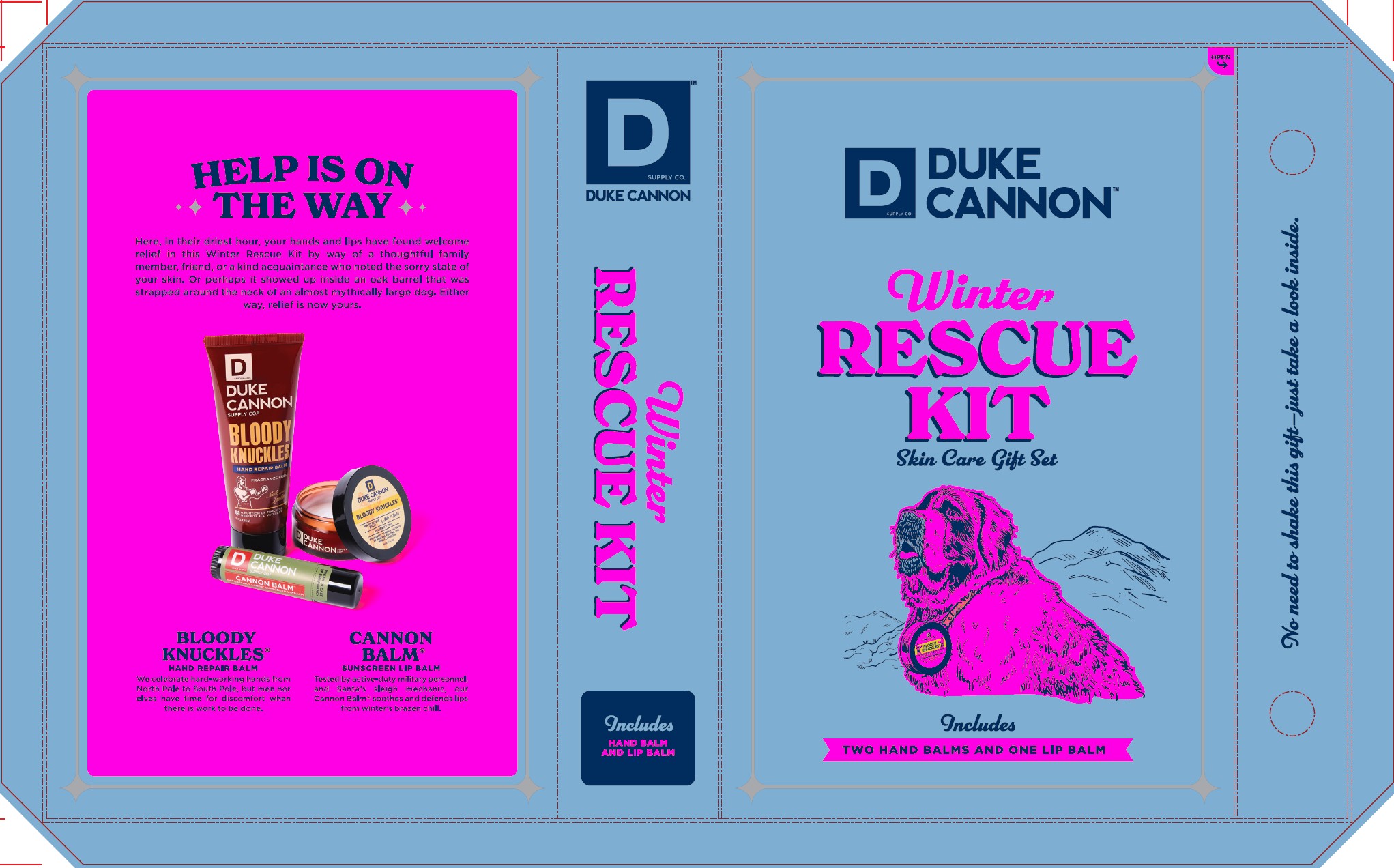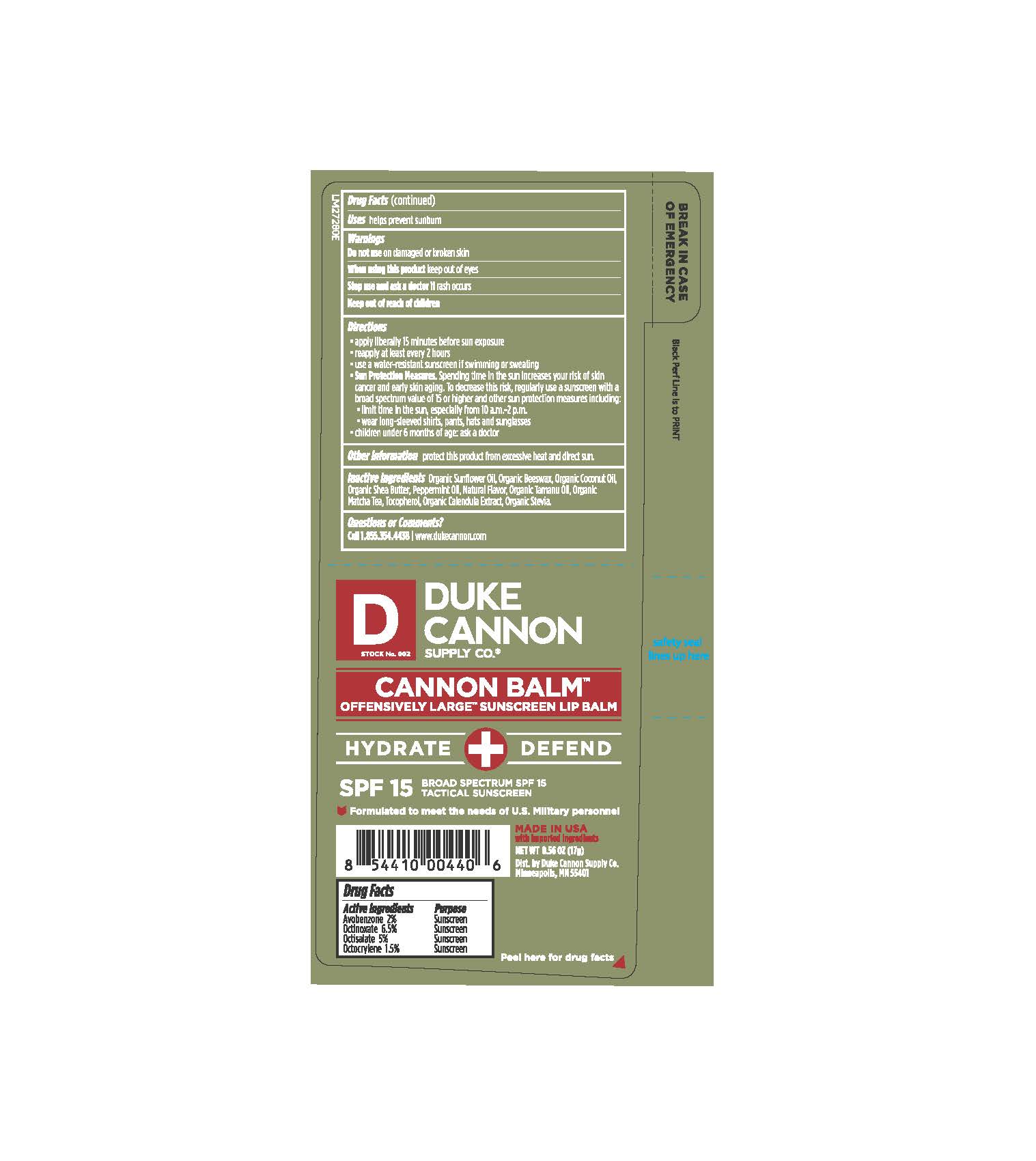 DRUG LABEL: Winter Rescue Kit
NDC: 71782-603 | Form: KIT | Route: TOPICAL
Manufacturer: Duke Cannon Supply Co.
Category: otc | Type: HUMAN OTC DRUG LABEL
Date: 20251015

ACTIVE INGREDIENTS: AVOBENZONE 0.34 g/17 g; OCTINOXATE 1.105 g/17 g; OCTOCRYLENE 0.255 g/17 g; OCTISALATE 0.85 g/17 g
INACTIVE INGREDIENTS: TAMANU OIL; SHEA BUTTER; CALENDULA OFFICINALIS FLOWER; STEVIA REBAUDIUNA LEAF; GREEN TEA LEAF; PEPPERMINT OIL; TOCOPHEROL; COCONUT OIL; SUNFLOWER OIL

Winter Rescue Kit

Drug Facts

ACTIVE INGREDIENT

Active ingredients | Purpose
Avobenzone 2% | Sunscreen
Octinoxate 6.5% | Sunscreen
Octisalate 5% | Sunscreen
Octocrylene 1.5% | Sunscreen

Uses

helps prevent sunburn

Warnings

Do not use

on damaged or broken skin

When using this product

keep out of eyes

Stop use and ask a doctor if

rash occurs

Keep out of reach of children

Directions

- apply liberally 15 minutes before sun exposure
- reapply at leaast every 2 hours
- use a water-resistant sunscreen if swimming or sweating
- Sun protection measures. Spending time in the sun increases your risk of skin cancer and early skin aging. To decrease this risk, regularly use a sunscreen with a broad spectrum of 15 or higher and other sun protection measures including:
- limit time in the sun, especially from 10 a.m. - 2 p.m.
- wear long-sleeved shirts, pants, hats, and sunglasses
- children under 6 months of age: ask a doctor

Other information

protect this product from excessive heat and direct sun

Inactive ingredients

organic sunflower oil, organic beeswax, organic coconut oil, organic shea butter, peppermint oil, natural flavor, organic tamanu oil, organic matcha tea, tocopherol, organic calendula extract, organic stevia

Questions or comments?

call 1.855.354.4438

www.dukecannon.com

Tube Label

DUKE

CANNON

SUPPLY CO.

CANNON BALM

OFFENSIVELY LARGE SUNSCREEN LIP BALM

HYDRATE+DEFEND

SPF 15 BROAD SPECTRUM SPF 15

TACTICAL SUNSCREEN

Formulated to meet the needs of U.S. Military personnel

MADE IN USA

with imported ingredients.

Net Wt 0.56 oz (17g)

Dist. by Duke Cannon Supply Co.

Minneapolis, MN 55401

Peel here for drug facts

Carton Label

DUKE CANNON

SUPPLY CO.

WINTER RESCUE KIT

Skin Care Gift Set